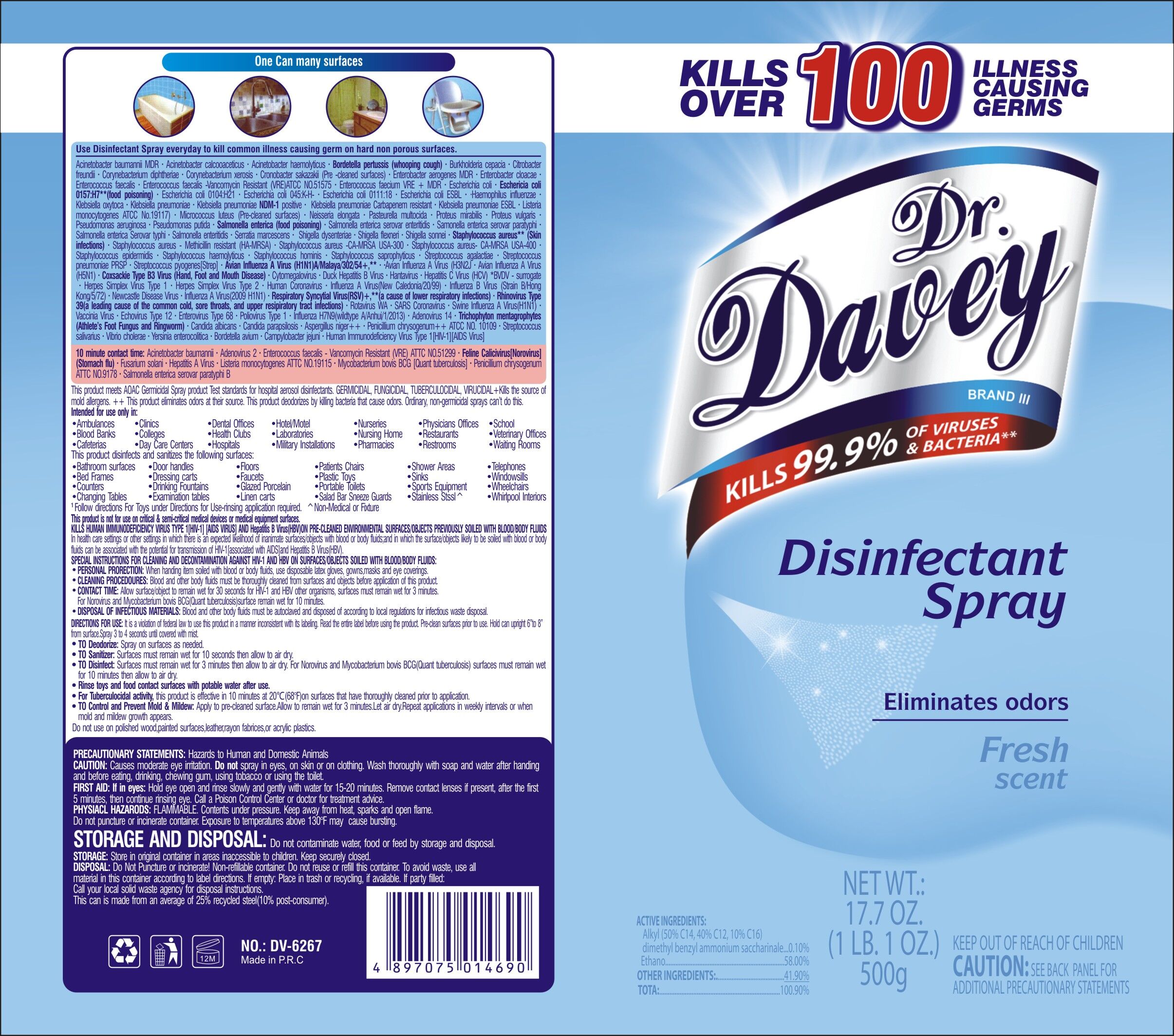 DRUG LABEL: Dr.Davey Alcohol Disinfectant
NDC: 74913-801 | Form: AEROSOL, SPRAY
Manufacturer: SHANTOU S.E.Z BAOJIE INDUSTRY CO., LTD
Category: otc | Type: HUMAN OTC DRUG LABEL
Date: 20201117

ACTIVE INGREDIENTS: ALCOHOL 75 g/100 g
INACTIVE INGREDIENTS: TROLAMINE 0.1 g/100 g; LIQUEFIED PETROLEUM GAS 24 g/100 g; CHLOROXYLENOL 0.5 g/100 g; SODIUM BENZOATE 0.4 g/100 g

Kills over 100 illness causing germs Dr.Davey Disinfectant Spray

Active Ingredient(s)

Alcohol 75% v/v. Purpose: Antiseptic

Purpose

Antiseptic

Warnings

For external use only. Flammable. Keep away from heat or flame

Do not use

- in children less than 2 months of age
- on open skin wounds

When using this product keep out of eyes, ears, and mouth. In case of contact with eyes, rinse eyes thoroughly with water.

Stop use and ask a doctor if irritation or rash occurs. These may be signs of a serious condition.

Keep out of reach of children. If swallowed, get medical help or contact a Poison Control Center right away.

Directions

Shake can well. Hold can 15-20cm from and then spray. Do Not use on skin,rayon acetate or satin fabric. Do not use on brass cooper and prolonged contact with aluminum. Do not allow prolonged to air dry. Surfaces may vary in quality-always test for suitablity on a small inconspicuous area prior to use. Do not use on polished wood painted surface or acrylic plastics.

Other information

- Store between 15-30C (59-86F)
- Avoid freezing and excessive heat above 40C (104F)

Inactive ingredients

Liquefied petroleum gas / Sodium Benzoate/ trolamine/ Chloroxylenol

DOSAGE AND ADMINISTRATION

Aerosol, Spray - An aerosol product which utilizes a compressed gas as the propellant to provide the force necessary to expel the product as a wet spray; it is applicable to solutions of medicinal agents in aqueous solvents.

RECENT MAJOR CHANGES

Aerosol, Spray - An aerosol product which utilizes a compressed gas as the propellant to provide the force necessary to expel the product as a wet spray; it is applicable to solutions of medicinal agents in aqueous solvents.

INDICATIONS AND USAGE

Shake can well. Hold can 15-20cm from and then spray. Do not use on skin, rayon acetate or statin fabric. Do not use on brass cooper and prolonged contact with aluminum. Do not allow prolonged to air dry. Surfaces may vary in quality-always test for suitability on a small inconspicuous area prior to use .Do not use on polished wood, painted surface or acrylic plastics.